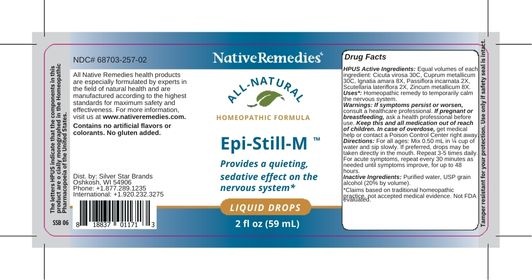 DRUG LABEL: Epi-Still-M
NDC: 68703-257 | Form: LIQUID
Manufacturer: Silver Star Brands
Category: homeopathic | Type: HUMAN OTC DRUG LABEL
Date: 20250101

ACTIVE INGREDIENTS: CICUTA VIROSA ROOT 30 [hp_C]/59 mL; STRYCHNOS IGNATII SEED 8 [hp_X]/59 mL; COPPER 30 [hp_C]/59 mL; PASSIFLORA INCARNATA FLOWER 2 [hp_X]/59 mL; SCUTELLARIA LATERIFLORA 2 [hp_X]/59 mL; ZINC 8 [hp_X]/59 mL
INACTIVE INGREDIENTS: ALCOHOL; WATER

NativeRemedies® Epi-Still-M™

HPUS Active Ingredients:

Each dose contains equal parts of: Cicuta virosa 30C, Cuprum metallicum 30C, Ignatia amara 8X, Passiflora incarnata 2X, Scutellaria lateriflora 2X, Zincum metallicum 8X.

Uses*:

Homeopathic medicine temporarily calms the nervous system.

*Claims based on traditional homeopathic practice, not accepted medical evidence. Not FDA evaluated.

Warnings:

If symptoms persist or worsen, consult a healthcare professional. If pregnant or breastfeeding, ask a health professional before use. Keep this and all medication out of reach of children. In case of overdose, get medical help or contact a Poison Control Center right away.

Directions:

For all ages: Mix 0.50 mL in 1/4 cup of water and sip slowly. Repeat 3-5 times daily. For acute symptoms, repeat every 30 minutes as needed until symptoms subside, or up to 48 hours. If preferred, drops may be taken directly in the mouth.

OTHER SAFETY INFORMATION

All Native Remedies health products are especially formulated by experts in the field of natural health and are manufactured according to the highest pharmaceutical standards for maximum safety and effectiveness. For more information, visit us at www.nativeremedies.com.

Contains no animal products, gluten, artificial flavors, preservatives, or colorants. Suitable for vegetarians.

Inactive Ingredients:

USP grain alcohol (20% by volume), purified water.

KEEP OUT OF REACH OF CHILDREN

Keep this and all medication out of reach of children. In case of overdose, get medical help or contact a Poison Control Center right away.

PREGNANCY OR BREAST FEEDING

If pregnant or breastfeeding, ask a healh professional before use.

PURPOSE

Provides a quieting, sedative effect on the nervous system.